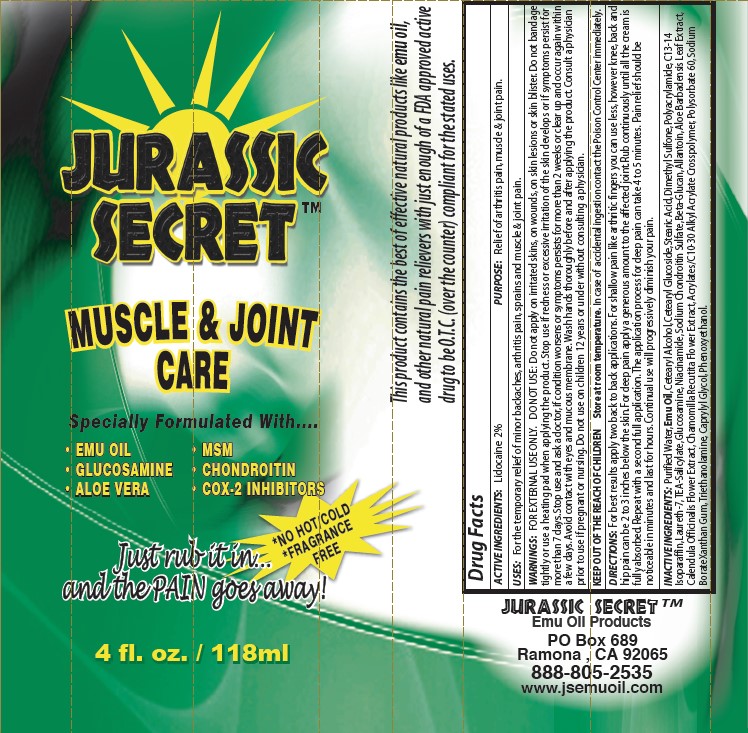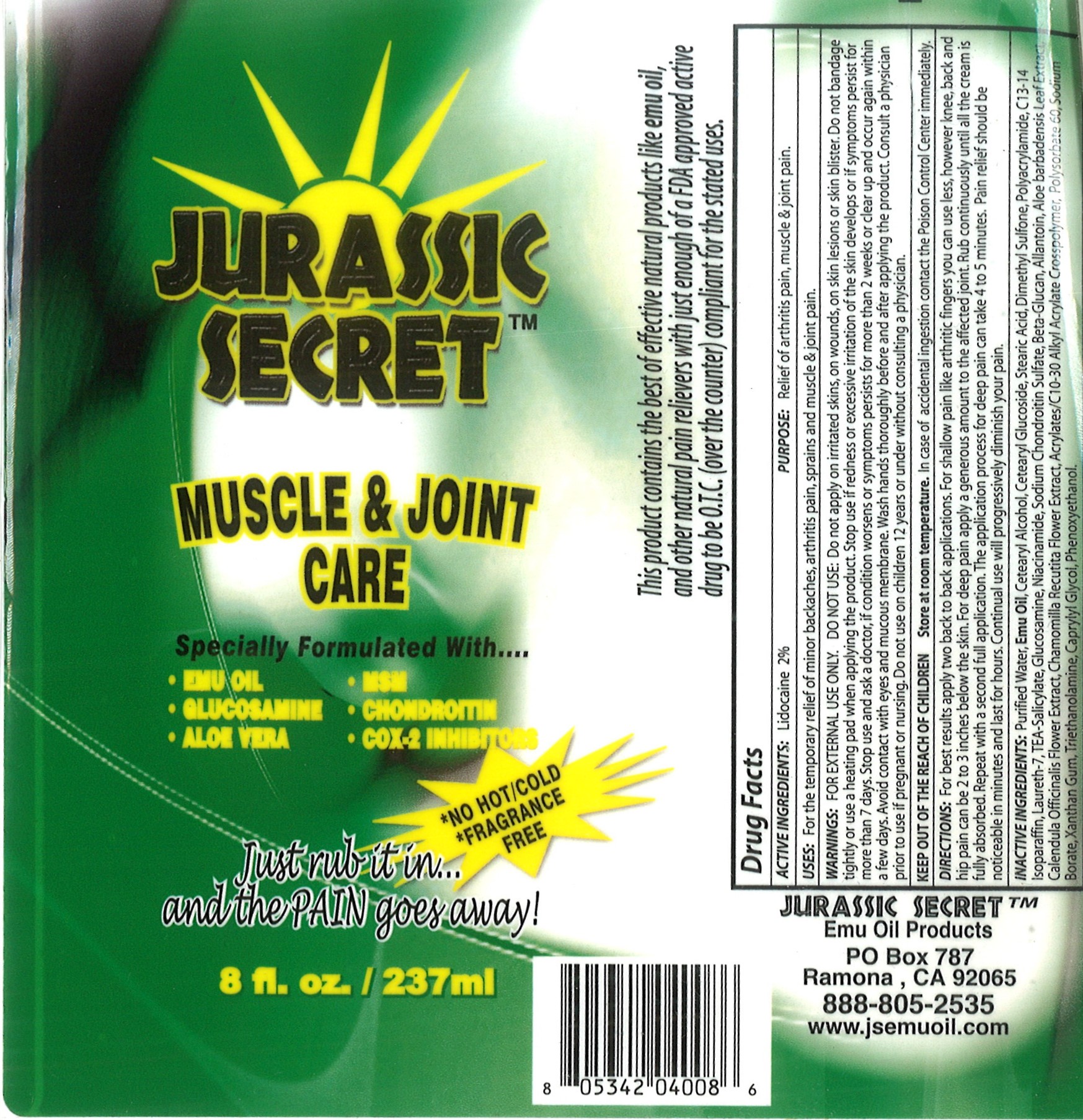 DRUG LABEL: Muscle and Joint Care
NDC: 67923-104 | Form: CREAM
Manufacturer: Vege Labs LLC.
Category: otc | Type: HUMAN OTC DRUG LABEL
Date: 20250311

ACTIVE INGREDIENTS: LIDOCAINE 2 mg/100 mg
INACTIVE INGREDIENTS: CHONDROITIN SULFATE SODIUM (BOVINE); 1,3-BETA-GLUCAN SYNTHASE COMPONENT FKS1; ALOE BARBADENSIS LEAF; PHENOXYETHANOL; CAPRYLYL GLYCOL; CALENDULA OFFICINALIS FLOWER; POLYACRYLAMIDE (10000 MW); TRIETHANOLAMINE; ALLANTOIN; EMU OIL; DIMETHYL SULFONE; CETEARYL GLUCOSIDE; STEARIC ACID; C13-14 ISOPARAFFIN; ACRYLATES/C10-30 ALKYL ACRYLATE CROSSPOLYMER (60000 MPA.S); SODIUM BORATE; XANTHAN GUM; NIACINAMIDE; TEA-SALICYLATE; LAURETH-7; GLUCOSAMINE; MATRICARIA RECUTITA; POLYSORBATE 60; WATER; CETEARYL ALCOHOL

ACTIVE INGREDIENTS

Lidocaine 2%

PURPOSE

Relief of artheritis pain, muscle & joint pain.

USES

For the temporary relief od minor backaches, arthritis pain, sprains and muscle & joint pain.

WARNINGS

FOR EXTERNAL USE ONLY. DO NOT USE: Do not apply on irritated skins, on wounds, on skin lesions or skin blister. Do not bandage
tightly or use a heating pad when applying the product. Stop use if redness or excessive irritation of the skin develops or if symptoms persist for more than 7 days. Stop use and ask a doctor, if condition worsens or symptoms persists for more than 2 weeks or clear up and occur again within a few days. Avoid contact with eyes and mucous membrane. Wash hands thoroughly before and after applying the product. Consult a physician prior to use if pregnant or nursing. Do not use on children 12 years or under without consulting a physician

DIRECTIONS

For best results apply two back to back applications. For shallow pain like arthritic fingers you can use less, however knee, back and
hip pain can be 2 to 3 inches below the skin. For deep pain apply a generous amount to the affected joint. Rub continuously until all the cream is fully absorbed. Repeat with a second full application. The application process for deep pain can take 4 to 5 minutes. Pain relief should be noticeable in minutes and last for hours. Continual use will progressively diminish your pain.

INACTIVE INGREDIENTS

Purified Water, Emu Oil, Cetearyl Alcohol, Cetearyl Glucoside, Stearic Acid, Dimethyl Sulfone, Polyacrylamide, C13-14 Isoparaffin, Laureth-7, TEA-Salicylate, Glucosamine, Niacinamide, Sodium Chondroitin Sulfate, Beta-Glucan, Allantoin, Aloe Barbadensis Leaf Extract, Calendula Officinalis Flower Extract, Chamomilla Recutita Flower Extract, Acrylates/C10-30 Alkyl Acrylate Crosspolymer, Polysorbate 60, Sodium BorateXanthan Gum, Triethanolamine, Caprylyl Glycol, Phenoxyethanol.